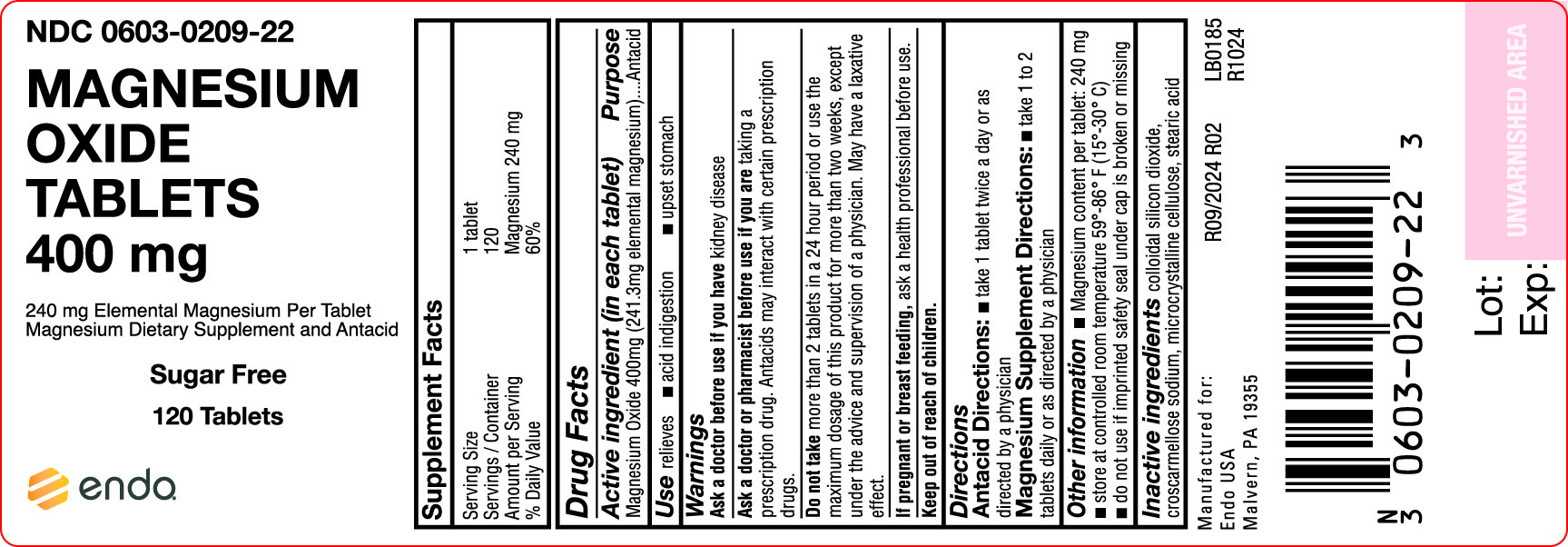 DRUG LABEL: Magnesium Oxide
NDC: 0603-0209 | Form: TABLET
Manufacturer: Endo USA
Category: otc | Type: HUMAN OTC DRUG LABEL
Date: 20200603

ACTIVE INGREDIENTS: MAGNESIUM OXIDE 400 mg/1 1
INACTIVE INGREDIENTS: SILICON DIOXIDE; CROSCARMELLOSE SODIUM; CELLULOSE, MICROCRYSTALLINE; STEARIC ACID

Magnesium Oxide Tablets

ACTIVE INGREDIENT (In each tablet)

Magnesium Oxide 400mg (240mg Elemental Magnesium)

Purpose

Antacid

USES

Relieves: ■ acid indigestion ■ upset stomach

WARNINGS

Ask a doctor if you have:

kidney disease

Ask a doctor or pharmacist before use if you are:

taking a prescription drug. Antacids may interact with certain prescription drugs.

Do not take

more than 2 tablets in a 24 hour period or use the maximum dosage of this product for more than two weeks, except under the advise and supervision of a physician. May have a laxative effect.

If pregnant or breast-feeding,

ask a health professional before use.

DIRECTIONS

Antacid Directions: ■ take 1 tablet twice a day or as directed by a physician

Magnesium Supplement Directions: ■ take 1 to 2 tablets daily or as directed by a physician

OTHER INFORMATION

■ Magnesium content per tablet: 240 mg ■ store at controlled room temperature 59°-86° F (15°-30°C) ■ do not use if imprinted safety seal under cap is broken or missing

INACTIVE INGREDIENTS

colloidal silicon dioxide, croscarmellose sodium, microcrystalline cellulose, stearic acid

PRINCIPAL DISPLAY PANEL

Magnesium Oxide 400mg